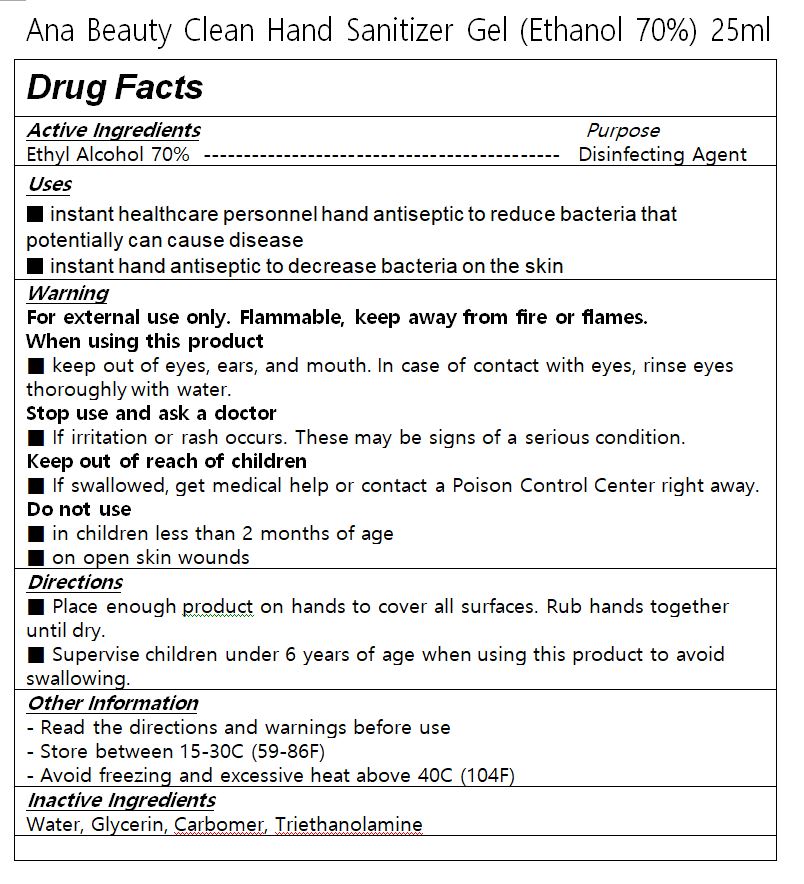 DRUG LABEL: ANA BEAUTY Clean Hand Sanitizer gel
NDC: 76770-0003 | Form: GEL
Manufacturer: COS&BIO Co Ltd
Category: otc | Type: HUMAN OTC DRUG LABEL
Date: 20200522

ACTIVE INGREDIENTS: ALCOHOL 70 mL/100 mL
INACTIVE INGREDIENTS: CARBOMER 940; GLYCERIN; WATER; TROLAMINE

Drug Facts

ACTIVE INGREDIENT

alcohol

INACTIVE INGREDIENT

Glycerin, Carbomer, Triethanolamine, Water

KEEP OUT OF REACH OF THE CHILDREN

PURPOSE

hand sanitizer to help reduce bacteria that potentially can cause disease

for use when soap and water are not available

INDICATIONS AND USAGE

Place enough product on hands to cover all surfaces.Rub hands together until dry.
Supervise children under 6 years of age when using this product to avoid swallowing.

WARNINGS

For external use only.

Flammable, keep away from fire or flame.

When using this product keep out of eyes. If contact with eyes occurs, rinse promptly and thoroughly with water.

Stop use and ask a doctor if significant irritation or sensitization develops.

Keep out of reach of children. If swallowed, get medical help or contact a Poison Control Center right away.

DOSAGE AND ADMINISTRATION

for external use only